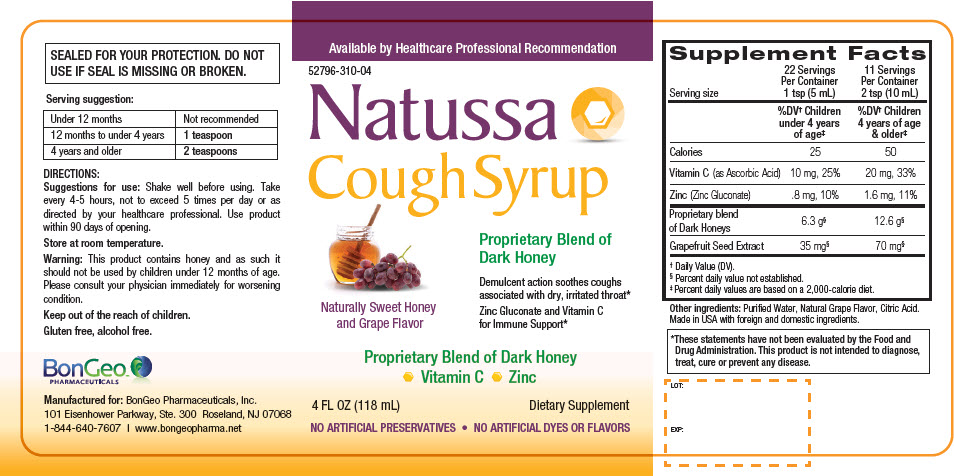 DRUG LABEL: Natussa Cough Syrup
NDC: 52796-310 | Form: LIQUID
Manufacturer: BonGeo Pharmaceuticals, Inc.
Category: other | Type: DIETARY SUPPLEMENT
Date: 20190131

ACTIVE INGREDIENTS: Ascorbic Acid 10 mg/5 mL; Zinc Gluconate 0.8 mg/5 mL; HONEY 6.3 g/5 mL; CITRUS PARADISI SEED 35 mg/5 mL
INACTIVE INGREDIENTS: Water; Citric Acid Monohydrate

Natussa Cough Syrup

STATEMENT OF IDENTITY

Supplement Facts
Serving size | 22 Servings Per Container 1 tsp (5 mL) | 11 Servings Per Container 2 tsp (10 mL)
 | %DV [Daily Value (DV).] Children under 4 years of age [Percent daily values are based on a 2,000-calorie diet.] | %DV Children 4 years of age & older
Calories | 25 | 50
Vitamin C (as Ascorbic Acid) | 10 mg, 25% | 20 mg, 33%
Zinc (Zinc Gluconate) | .8 mg, 10% | 1.6 mg, 11%
Proprietary blend of Dark Honeys | 6.3 g [Percent daily value not established.] | 12.6 g
Grapefruit Seed Extract | 35 mg | 70 mg

Other ingredients: Purified Water, Natural Grape Flavor, Citric Acid.

Made in USA with foreign and domestic ingredients.

HEALTH CLAIM

*These statements have not been evaluated by the Food and Drug Administration. This product is not intended to diagnose, treat, cure or prevent any disease.

HEALTH CLAIM

LOT:

EXP:

HEALTH CLAIM

SEALED FOR YOUR PROTECTION. DO NOT USE IF SEAL IS MISSING OR BROKEN.

Serving suggestion

Under 12 months | Not recommended
12 months to under 4 years | 1 teaspoon
4 years and older | 2 teaspoons

DIRECTIONS

Suggestions for use

Shake well before using. Take every 4-5 hours, not to exceed 5 times per day or as directed by your healthcare professional. Use product within 90 days of opening.

Store at room temperature.

Warning

This product contains honey and as such it should not be used by children under 12 months of age. Please consult your physician immediately for worsening condition.

Keep out of the reach of children.

Gluten free, alcohol free.

HEALTH CLAIM

Manufactured for: BonGeo Pharmaceuticals, Inc.
101 Eisenhower Parkway, Ste. 300 Roseland, NJ 07068
1-844-640-7607 | www.bongeopharma.net

PRINCIPAL DISPLAY PANEL - 118 mL Bottle Label

Available by Healthcare Professional Recommendation

52796-310-04

Natussa
Cough Syrup

Naturally Sweet Honey
and Grape Flavor

Proprietary Blend of
Dark Honey

Demulcent action soothes coughs
associated with dry, irritated throat*

Zinc Gluconate and Vitamin C
for Immune Support*

Proprietary Blend of Dark Honey
• Vitamin C • Zinc

4 FL OZ (118 mL)
Dietary Supplement

NO ARTIFICIAL PRESERVATIVES • NO ARTIFICIAL DYES OR FLAVORS